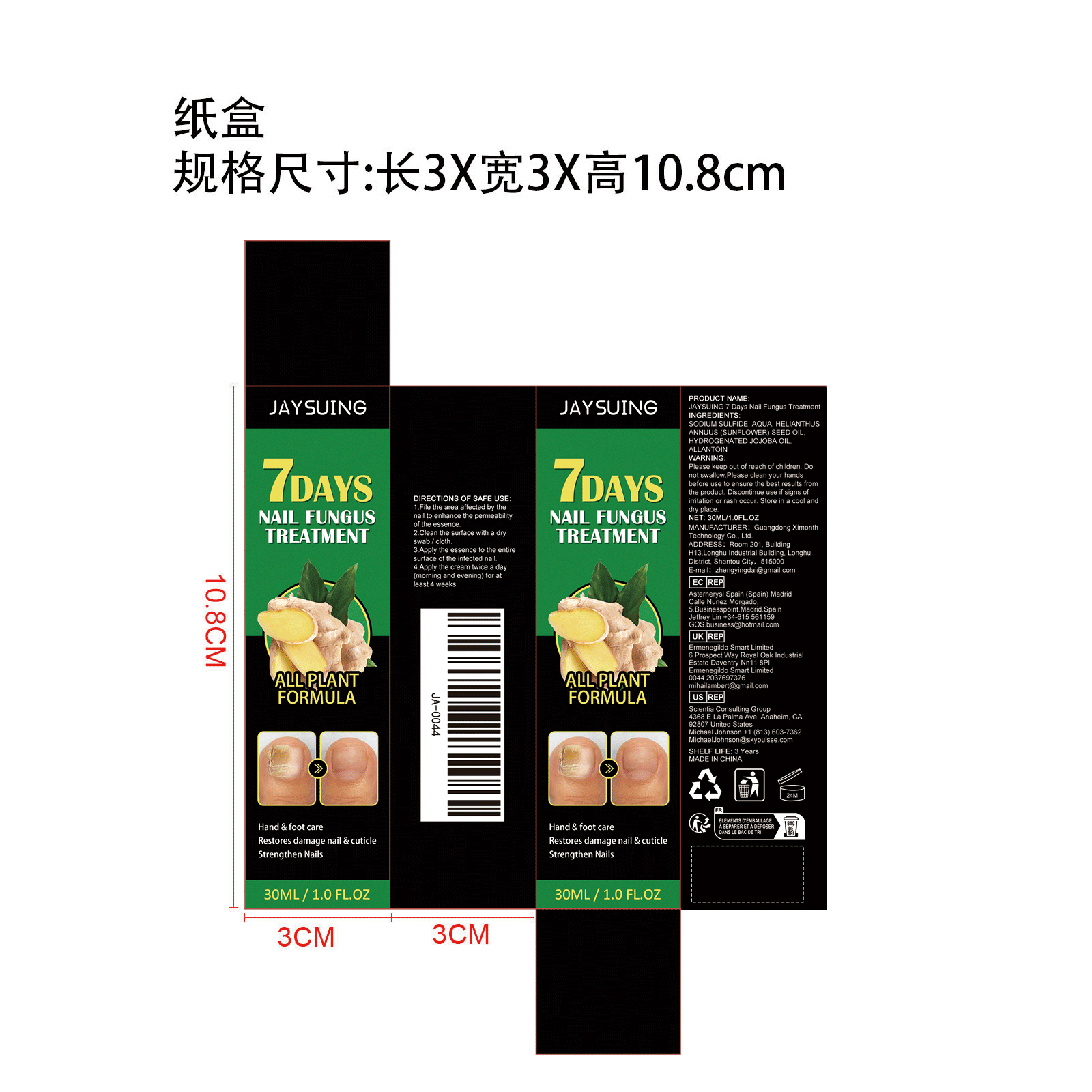 DRUG LABEL: 7 Days Nail Fungus Treatment
NDC: 84660-010 | Form: LIQUID
Manufacturer: Guangdong Ximonth Technology Co., Ltd.
Category: otc | Type: HUMAN OTC DRUG LABEL
Date: 20240906

ACTIVE INGREDIENTS: HYDROGENATED JOJOBA OIL 6 mg/30 mg; SUNFLOWER OIL 3 mg/30 mg
INACTIVE INGREDIENTS: ALLANTOIN 4.5 mg/30 mg; WATER 9 mL/30 mg; SODIUM SULFIDE ANHYDROUS 7.5 mg/30 mg

Active Ingredient(s)

HELIANTHUS ANNUUS (SUNFLOWER) SEED OIL,HYDROGENATED JOJOBA OIL,ALLANTOIN,SODIUM SULFIDE

Purpose

Restores damage nail & cuticle

Use

1.File the area affected by the nail to enhance the permeability of the essence.2.Clean the surface with a dry swab /cloth.3.Apply the essence to the entire surface of the infected nail.4.Apply the cream twice a day (morning and evening) for at least 4 weeks.

Warnings

Please keep out of reach of children.Do not swallow.Please clean your hands before use to ensure the best results from the product.Discontinue use if signs of irritation or rash occur.Store in a cool and dry place.

Do not use

Discontinue use if signs of irritation or rash occur.

STOP USE

Discontinue use if signs of irritation or rash occur.

KEEP OUT OF REACH OF CHILDREN

Please keep out of reach of children. Do not swallow.

STORAGE AND HANDLING

Avoid freezing and excessive heat above 40C (104F) ）

Store in a cool and dry place.

INACTIVE INGREDIENT

AQUA